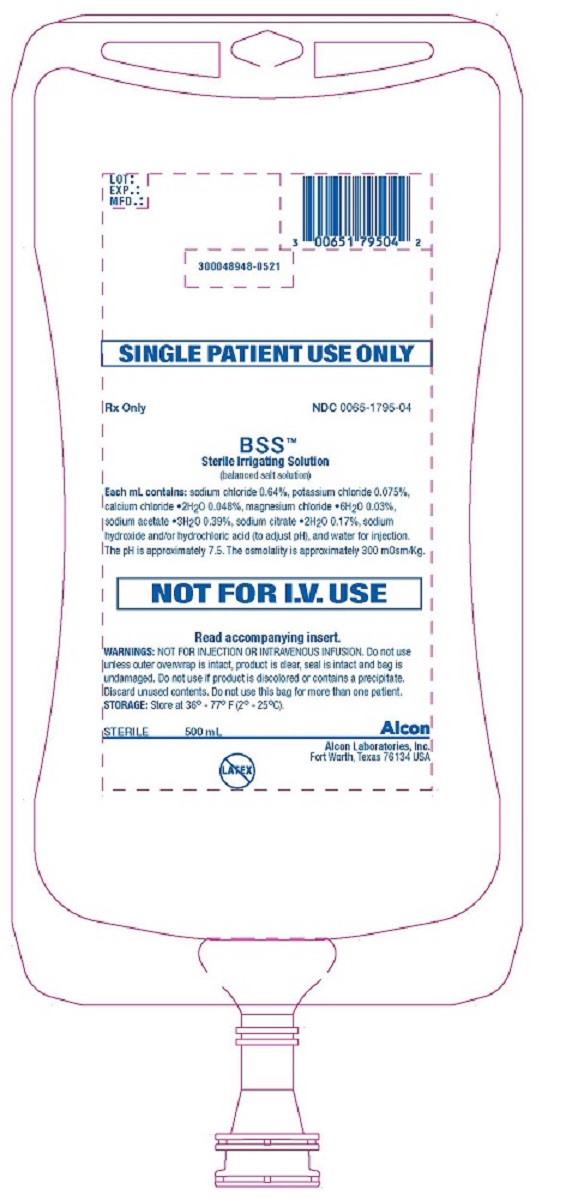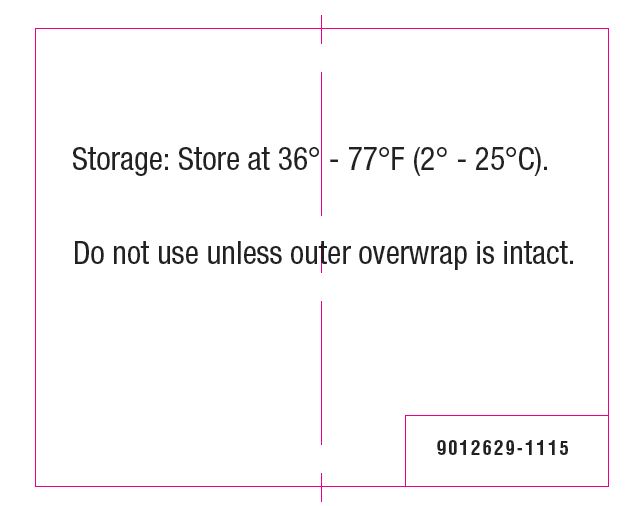 DRUG LABEL: BSS 
NDC: 0065-1795 | Form: SOLUTION
Manufacturer: Alcon Laboratories, Inc.
Category: prescription | Type: HUMAN PRESCRIPTION DRUG LABEL
Date: 20231214

ACTIVE INGREDIENTS: SODIUM CHLORIDE 6.4 mg/1 mL; POTASSIUM CHLORIDE 0.75 mg/1 mL; CALCIUM CHLORIDE 0.48 mg/1 mL; MAGNESIUM CHLORIDE 0.3 mg/1 mL; SODIUM ACETATE 3.9 mg/1 mL; SODIUM CITRATE 1.7 mg/1 mL
INACTIVE INGREDIENTS: SODIUM HYDROXIDE; HYDROCHLORIC ACID; WATER

BSS™
Sterile Irrigating Solution
(balanced salt solution)

DESCRIPTION:

BSS™ Sterile Irrigating Solution is a sterile balanced salt solution, each mL containing sodium chloride (NaCl) 0.64%, potassium chloride (KCl) 0.075%, calcium chloride dihydrate (CaCl2•2H2O) 0.048%, magnesium chloride hexahydrate (MgCl2•6H2O) 0.03%, sodium acetate trihydrate (C2H3NaO2•3H2O) 0.39%, sodium citrate dihydrate (C6H5Na3O7•2H2O) 0.17%, sodium hydroxide and/or hydrochloric acid (to adjust pH), and water for injection. The pH is approximately 7.5. The osmolality is approximately 300 mOsm/Kg.

CLINICAL PHARMACOLOGY:

BSS Sterile Irrigating Solution is an isotonic solution for use in irrigating tissues of the eyes.

INDICATIONS AND USAGE:

For use as an extraocular and intraocular irrigating solution during ocular surgical procedure involving perfusion of the eye with an expected maximum duration of less than 60 minutes.

WARNINGS:

- NOT FOR INJECTION OR INTRAVENOUS INFUSION.
- Do not use unless product is clear, seal is intact, and container is undamaged.
- Do not use if product is discolored or contains a precipitate.
- SINGLE patient use only. The contents of this bag should not be used in more than one patient.
- This solution contains no preservative, unused contents should be discarded.

PRECAUTIONS:

Open under aseptic conditions only.

Studies suggest that intraocular irrigating solutions which are iso-osmotic with normal aqueous fluids should be used with caution in diabetic patients undergoing vitrectomy since intraoperative lens changes have been observed.

There have been reports of corneal clouding and edema following ocular surgery in which BSS Sterile Irrigating Solution was used as an irrigating solution.

ADVERSE REACTIONS:

Irrigation or any other trauma to the corneal endothelium may result in corneal swelling or bullous keratopathy.

Post-operative inflammatory reactions as well as incidents of corneal edema and corneal decompensation have been reported.

DOSAGE AND ADMINISTRATION:

This irrigating solution should be used according to standard format for each surgical procedure. Follow directions of the particular administration set to be used. Remove the outer overwrap. Clean and disinfect the rubber stopper by using a sterile alcohol wipe. Insert the spike aseptically into the bag through the target area of the rubber stopper. Allow the fluid to flow and remove air from the tubing before irrigation begins.

HOW SUPPLIED:

BSS™ Sterile Irrigating Solution is supplied in a clear polypropylene bag using a grey butyl stopper and aluminum seal packaged in a clear, multilayered plastic outer overwrap.
500 mL in a bag: NDC 0065-1795-04.

STORAGE: Store at 36° - 77°F (2° - 25°C).

Alcon
Distributed by:
Alcon Laboratories, Inc.
Fort Worth, Texas 76134 USA
© 2021 Alcon, Inc.

PRINCIPAL DISPLAY PANEL

SINGLE PATIENT USE ONLY
Rx Only
NDC 0065-1795-04
BSS™
Sterile Irrigating Solution
(balanced salt solution)
Each mL contains: sodium chloride 0.64%, potassium chloride 0.075%, calcium chloride •2H2O 0.048%, magnesium chloride •6H2O 0.03%, sodium acetate •3H2O 0.39%, sodium citrate •2H2O 0.17%, sodium hydroxide and/or hydrochloric acid (to adjust pH), and water for injection. The pH is approximately 7.5. The osmolality is approximately 300 mOsm/Kg.
NOT FOR I.V. USE
Read accompanying insert.
WARNINGS: NOT FOR INJECTION OR INTRAVENOUS INFUSION. Do not use unless outer overwrap is intact, product is clear, seal is intact and bag is undamaged. Do not use if product is discolored or contains a precipitate. Discard unused contents. Do not use this bag for more than one patient.
STORAGE: Store at 36° - 77° F (2° - 25°C).
STERILE 500 mL
Alcon
Alcon Laboratories, Inc.
Fort Worth, Texas 76134 USA
LOT:
EXP.:
MFD.:
300048948-0521

Storage: Store at 36° - 77°F (2° - 25°C).
Do not use unless outer overwrap is intact.
9012629-1115